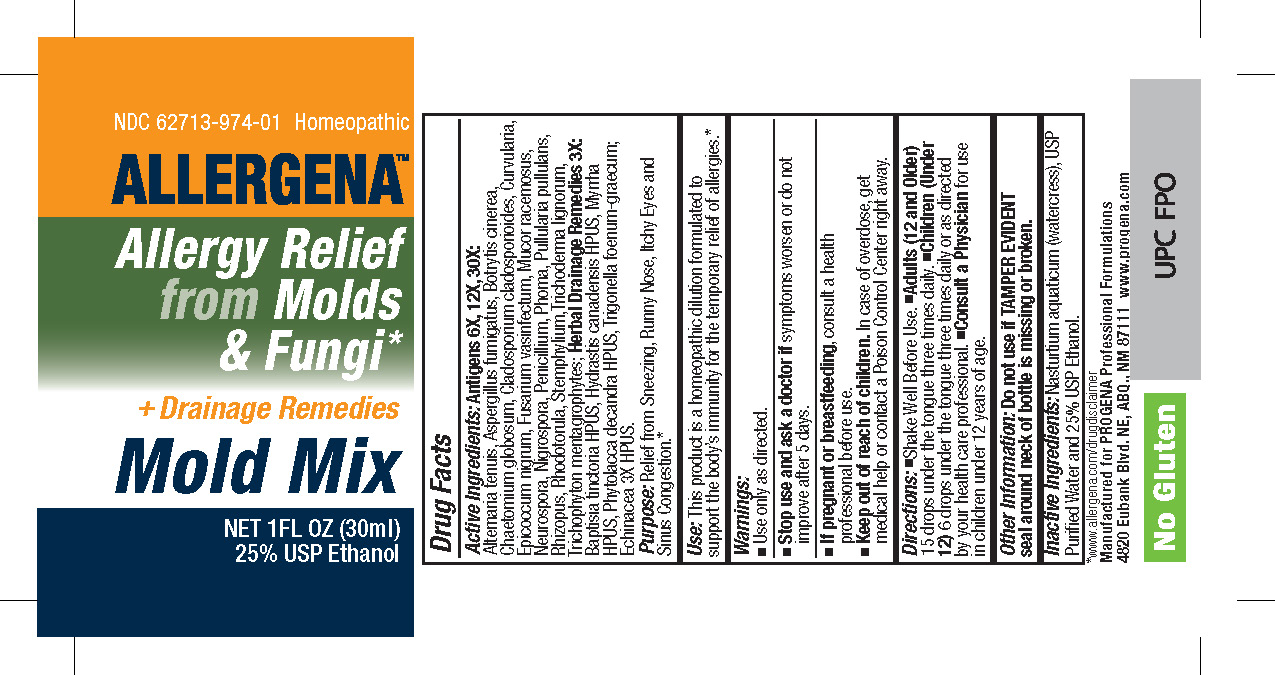 DRUG LABEL: Allergena Mold Mix
NDC: 62713-974 | Form: LIQUID
Manufacturer: Meditrend, Inc. DBA Progena Professional Formulations
Category: homeopathic | Type: HUMAN OTC DRUG LABEL
Date: 20250130

ACTIVE INGREDIENTS: ALTERNARIA ALTERNATA 30 [hp_X]/1 mL; ASPERGILLUS FUMIGATUS 30 [hp_X]/1 mL; AUREOBASIDIUM PULLULANS VAR. PULLUTANS 30 [hp_X]/1 mL; BOTRYTIS CINEREA 30 [hp_X]/1 mL; CHAETOMIUM GLOBOSUM 30 [hp_X]/1 mL; CLADOSPORIUM CLADOSPORIOIDES 30 [hp_X]/1 mL; COCHLIOBOLUS SPICIFER 30 [hp_X]/1 mL; EPICOCCUM NIGRUM 30 [hp_X]/1 mL; FUSARIUM OXYSPORUM VASINFECTUM 30 [hp_X]/1 mL; MUCOR RACEMOSUS 30 [hp_X]/1 mL; NEUROSPORA SITOPHILA 30 [hp_X]/1 mL; KHUSKIA ORYZAE 30 [hp_X]/1 mL; PENICILLIUM CHRYSOGENUM VAR. CHRYSOGENUM 30 [hp_X]/1 mL; PHOMA EXIGUA VAR. EXIGUA 30 [hp_X]/1 mL; RHIZOPUS STOLONIFER 30 [hp_X]/1 mL; RHODOTORULA RUBRA 30 [hp_X]/1 mL; STEMPHYLIUM SARCINIFORME 30 [hp_X]/1 mL; TRICHODERMA VIRIDE 30 [hp_X]/1 mL; TRICHOPHYTON MENTAGROPHYTES 30 [hp_X]/1 mL; BAPTISIA TINCTORIA ROOT 3 [hp_X]/1 mL; GOLDENSEAL 3 [hp_X]/1 mL; MYRRH 3 [hp_X]/1 mL; PHYTOLACCA AMERICANA ROOT 3 [hp_X]/1 mL; FENUGREEK LEAF 3 [hp_X]/1 mL; ECHINACEA, UNSPECIFIED 3 [hp_X]/1 mL
INACTIVE INGREDIENTS: WATER; ALCOHOL; NASTURTIUM OFFICINALE

Allergena Mold Mix

ACTIVE INGREDIENT

Active Ingredients: Antigens 6X, 12X, 30X:Alternaria Tenuis, Aspergillus fumigatus, Botrytis cinerea, Chaetomium globosum, Cladosporium cladosporioides, Curvularia, Epicoccum nigrum, Fusarium vasinfectum, Mucor racemosus, Neurospora, Nigrospora, Penicillium, Phoma, Pullularia pullulans, Rhizopus, Rhodotorula, Stemphylium, Trichoderma lignorum, Trichophyton mentagrophytes. Herbal Drainage Remedies 3X:Baptisia tinctoria HPUS, Hydrastis canadensis HPUS, Myrrha HPUS, Phytolacca decandra HPUS, Trigonella foenum-graecum;Echinacea 3X HPUS.

PURPOSE

Purpose:Relief from Sneezing, Runny Nose, Itchy Eyes and Sinus Congestion.*

INDICATIONS AND USAGE

Use:This product is a homeopathic dilution formulated to support the body's immunity for the temporary relief of allergies.*

Keep Out of Reach of Children.In case of overdose, get medical help or contact a Poison Control Center right away.

Warnings:

- Use Only as directed.
- Stop use and ask a doctor ifsymptoms worsen or do not improve after 5 days.
- If pregnant or breastfeeding, consult a health professional before use.

DOSAGE AND ADMINISTRATION

Directions:•Shake Well Before Use. • Adults (12 and Older)15 drops under the tongue three times daily. • Children (Under 12)6 drops under the tongue three times daily or as directed by your health care professional. • Consult a Physicianfor use in children under 12 years of age.

Other Information: Do not use if TAMPER EVIDENT seal around neck of bottle is missing or broken.

INACTIVE INGREDIENT

Inactive Ingredients: Nasturtium aquaticum (watercress), USP Purified water and 25% USP Ethanol.

PACKAGE LABEL

*www.allergena.com/drugdisclaimer
Manufactured for PROGENA Professional Formulations
4820 Eubank Blvd. NE, ABQ, NM 87111 www.allergena.com